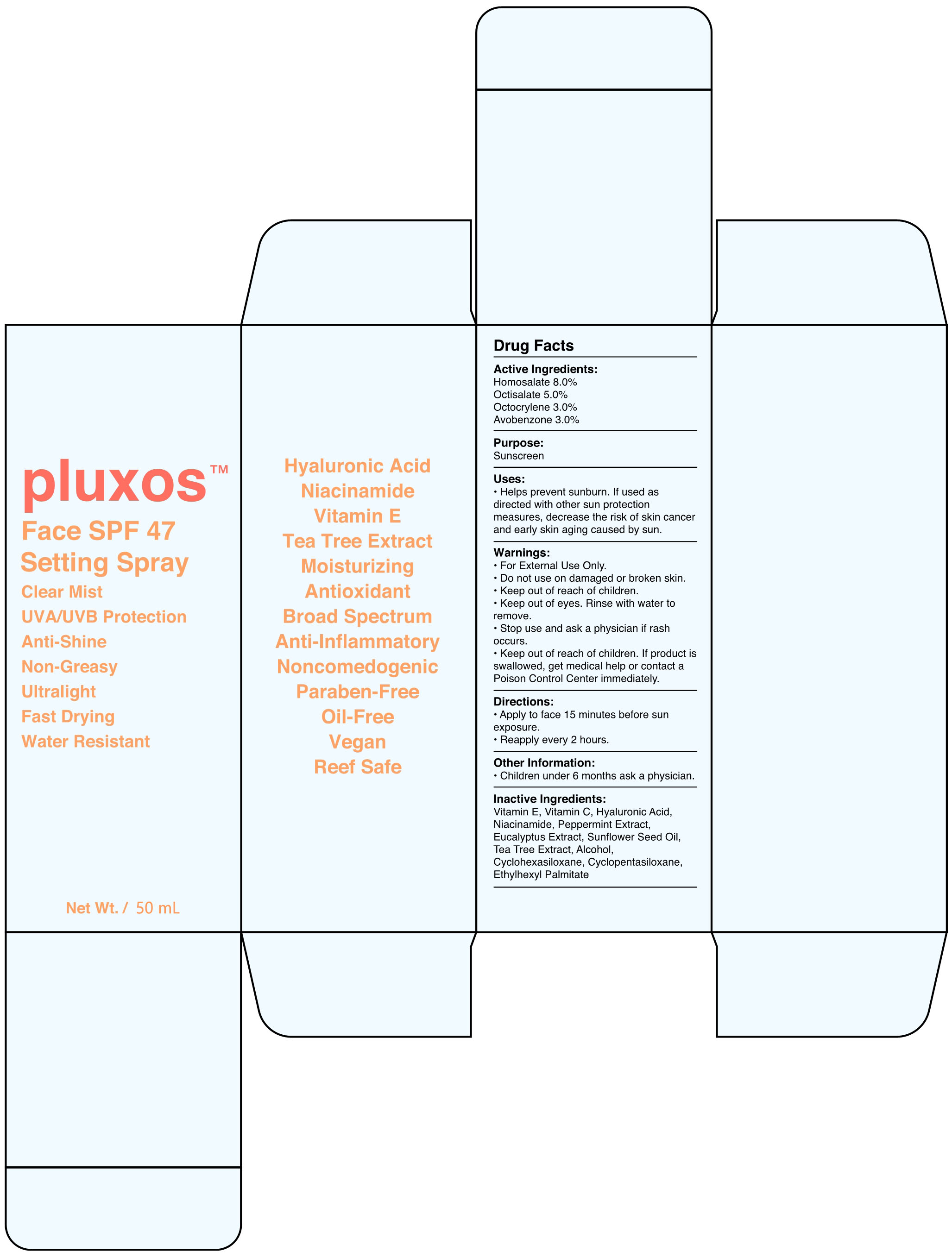 DRUG LABEL: Face SPF 47 Setting
NDC: 82723-001 | Form: SPRAY
Manufacturer: Aopline Health Industry Technology (Guangzhou) Co., Ltd.
Category: otc | Type: HUMAN OTC DRUG LABEL
Date: 20250108

ACTIVE INGREDIENTS: OCTOCRYLENE 3 g/100 mL; AVOBENZONE 3 g/100 mL; OCTISALATE 5 g/100 mL; HOMOSALATE 8 g/100 mL
INACTIVE INGREDIENTS: EUCALYPTUS GLOBULUS LEAF; SUNFLOWER OIL; ALCOHOL; CYCLOMETHICONE 6; MELALEUCA ALTERNIFOLIA LEAF; ETHYLHEXYL PALMITATE; ALPHA-TOCOPHEROL; HYALURONIC ACID; PEPPERMINT; CYCLOMETHICONE 5; NIACINAMIDE; ASCORBIC ACID

82723-001
Face SPF 47 Setting Spray

Active Ingredients

Homosalate 8.0%

Octisalate 5.0%

Octocrylene 3.0%

Avobenzone 3.0%

Purpose

Sunscreen

Uses

Helps prevent sunburn. If used as directed with other sun protection measures, decrease the risk of skin cancer and early skin aging caused by sun.

Warnings

For External Use Only.

Do not use on damaged or broken skin.

Keep out of reach of children.

Keep out of eyes. Rinse with water to remove.

Stop use and ask a physician if rash occurs.

Keep out of reach of children . If product is swallowed, get medical help or contact a Poison Control Center immediately.

Directions

•Apply to face 15 minutes before sun exposure.

Reapply every 2 hours.

Other Information

Children under 6 months ask a physician.

Inactive Ingredients

Vitamin E, Vitamin C, Hyaluronic Acid, Niacinamide, Peppermint Extract, Eucalyptus Extract, Sunflower Seed Oil, Tea Tree Extract, Alcohol, Cyclohexasiloxane, Cyclopentasiloxane, Ethylhexyl Palmitate

Keep out of reach of children.

Stop use

Stop use and ask a physician if rash occurs.

WHEN USING

For External Use Only.

Do not use on damaged or broken skin.

Keep out of reach of children.

Keep out of eyes. Rinse with water to remove.

Stop use and ask a physician if rash occurs.

Keep out of reach of children . If product is swallowed, get medical help or contact a Poison Control Center immediately.

Do not use on damaged or broken skin.